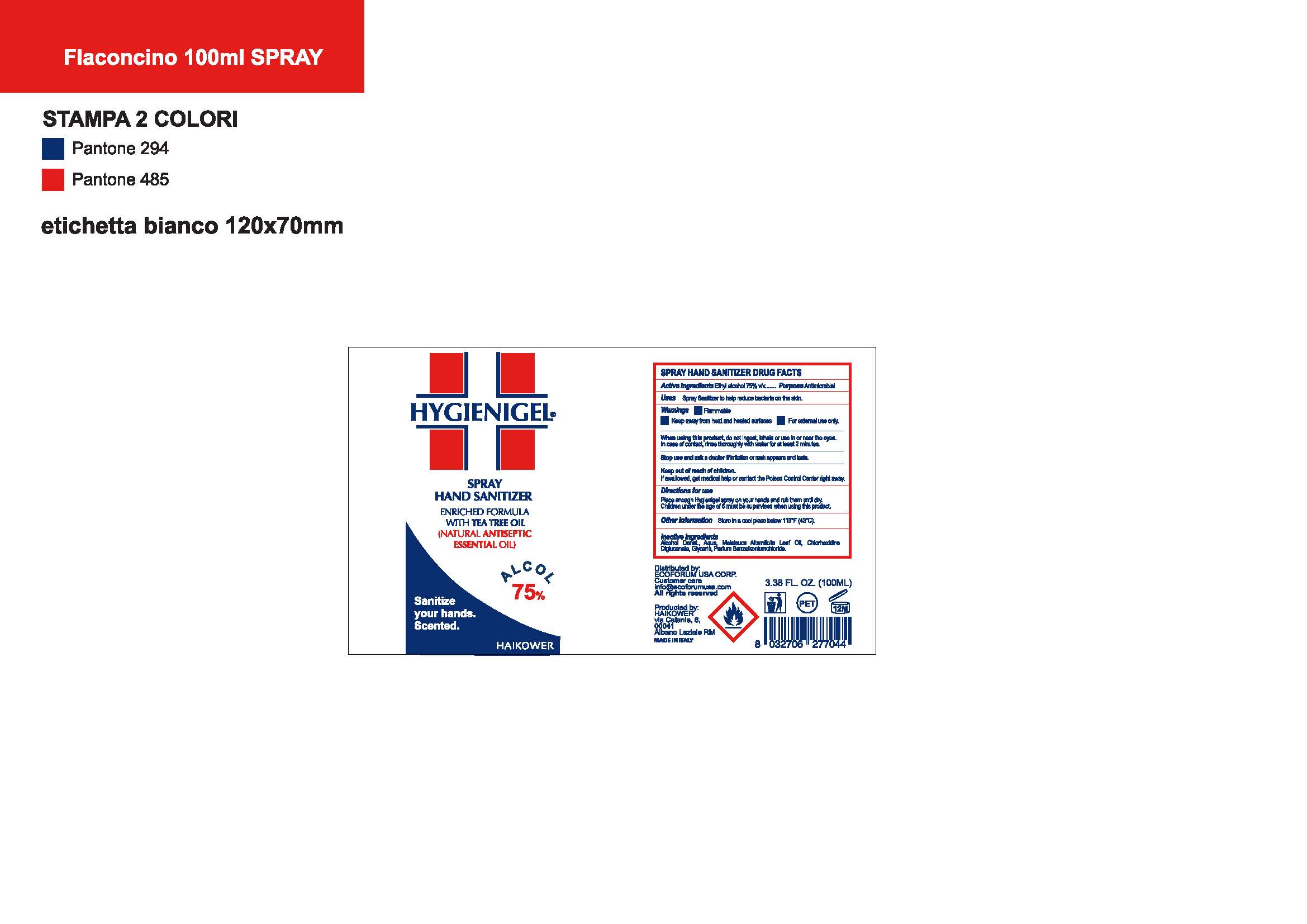 DRUG LABEL: Hygienigel
NDC: 78619-100 | Form: SOLUTION, GEL FORMING / DROPS
Manufacturer: HAIKOWER S.r.l.
Category: otc | Type: HUMAN OTC DRUG LABEL
Date: 20210226

ACTIVE INGREDIENTS: ALCOHOL 75 mL/100 mL
INACTIVE INGREDIENTS: MELALEUCA ALTERNIFOLIA LEAF; BENZALKONIUM CHLORIDE; CHLORHEXIDINE GLUCONATE; GLYCERIN; WATER

Hygienigel 75% Spray

Dosage and Admin

Place enough HYGIENIGEL on your hands and rub them until dry.

Children under 6 years of age must be supervised when using HYGIENIGEL.

Inactive Ingredients

Water, Melaleuca Alternifolia Leaf Oil, Chlorhexidine Digluconate, Grlycerin, BEnzalkonium Chloride

OTC - Active ingredient

Ethyl Alcohol 75% v/v

OTC - Ask Doctor section

Stop use and ask a doctor if irritation or rash appears and lasts.

OTC - Do not use

When using this product, do not ingest, inhale or use in or near the eyes. In case of contact, rinse thoroughly with water for at least 2 minutes.

OTC - Keep out of reach of children

Keep out of reach of children.

If swallowed, get medical help or contact the Poison Control Center right away.

OTC - Purpose

Uses Hand Sanitizer to help reduce bacteria on the skin

Indication and usage

Uses Hand Sanitizer to help reduce bacteria on the skin

OTC _ Stop Use

Stop use and ask a doctor if irritation or rash appears and lasts.

When using this product, do not ingest, inhale or use in or near the eyes. In case of contact, rinse thoroughly with water for at least 2 minutes.

Warnings

- Flammable.

- Keep away from flame and fire.

- For external use only.